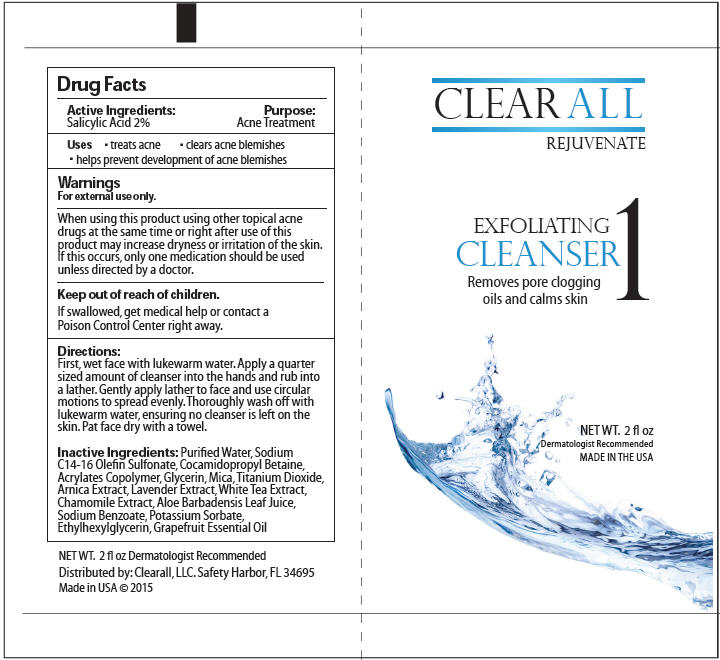 DRUG LABEL: Exfoliating Cleanser
NDC: 62248-120 | Form: LOTION
Manufacturer: Clearall LLC
Category: otc | Type: HUMAN OTC DRUG LABEL
Date: 20150420

ACTIVE INGREDIENTS: Salicylic Acid 20 mg/1 mL
INACTIVE INGREDIENTS: WATER; SODIUM C14-16 OLEFIN SULFONATE; COCAMIDOPROPYL BETAINE; METHACRYLIC ACID - ETHYL ACRYLATE COPOLYMER (4500 MPA.S); GLYCERIN; MICA; TITANIUM DIOXIDE; ARNICA MONTANA; LAVANDULA ANGUSTIFOLIA FLOWER; WHITE TEA; CHAMOMILE; ALOE VERA LEAF; SODIUM BENZOATE; POTASSIUM SORBATE; ETHYLHEXYLGLYCERIN; GRAPEFRUIT OIL

Exfoliating Cleanser

Active Ingredients

Salicylic Acid 2%

Purpose

Acne Treatment

Uses

- treats acne
- clears acne blemishes
- helps prevent development of acne blemishes

Warnings

For external use only.

When using this product using other topical acne drugs at the same time or right after use of this product may increase dryness or irritation of the skin. If this occurs, only one medication should be used unless directed by a doctor.

Keep out of reach of children.

If swallowed, get medical help or contact a Poison Control Center right away.

Directions

First, wet face with lukewarm water. Apply a quarter sized amount of cleanser into the hands and rub into a lather. Gently apply lather to face and use circular motions to spread evenly. Thoroughly wash off with lukewarm water, ensuring no cleanser is left on the skin. Pat face dry with a towel.

Inactive Ingredients

Purified Water, Sodium C14-16 Olefin Sulfonate, Cocamidopropyl Betaine, Acrylates Copolymer, Glycerin, Mica, Titanium Dioxide, Arnica Extract, Lavender Extract, White Tea Extract, Chamomile Extract, Aloe Barbadensis Leaf Juice, Sodium Benzoate, Potassium Sorbate, Ethylhexylglycerin, Grapefruit Essential Oil

Distributed by: Clearall, LLC. Safety Harbor, FL 34695

PRINCIPAL DISPLAY PANEL - 2 fl oz Tube Label

CLEAR ALL
REJUVENATE

EXFOLIATING
CLEANSER
Removes pore clogging
oils and calms skin
1

NET WT. 2 fl oz
Dermatologist Recommended
MADE IN THE USA